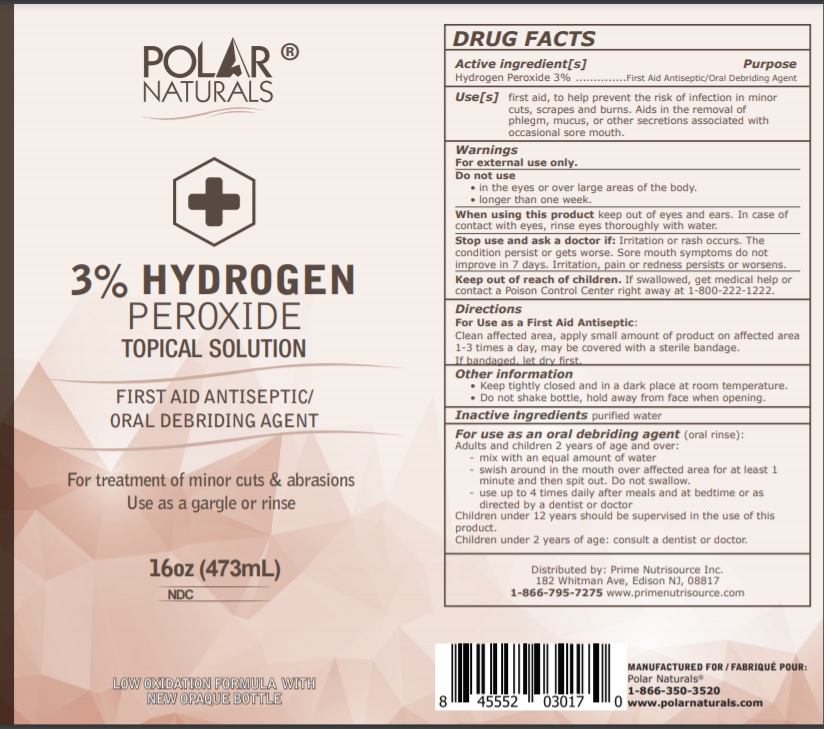 DRUG LABEL: BENEMAX ADVANCED Hand Sanitizer
NDC: 73700-003 | Form: LIQUID
Manufacturer: Nugale Pharmaceutical Inc
Category: otc | Type: HUMAN OTC DRUG LABEL
Date: 20210311

ACTIVE INGREDIENTS: HYDROGEN PEROXIDE 3 mL/100 mL
INACTIVE INGREDIENTS: WATER

Drug Facts

Active ingredient

Hydrogen peroxide 3%

Purpose

Antiseptic

Warnings

For external use only. Do not use: In the eyes over large areas of the body, or for longer than 1 week. Ask a doctor before use if you have deep puncture wounds, animal bites or serious burns.

Stop use immediately and consult your physician if: The condition persists or worsens after use. If sore mouth symptoms do not improve in 7 days, If irritation, pain or redness persist or worsen. If swelling, rash or fever develop.

Uses

First aid to help prevent the risk of infection in minor cuts, scrapes and burns. Aids in the removal of phlegm, mucous or other secretions associated with occasional sore mouth.

Directions

• clean the affected area • apply a small amount of product on affected area 1 to 3 times a day • may be covered with a sterile bandage • if
bandaged, let dry first • children under 12 years of age should be supervised in the use of this product. • children under 2 years of age: consult a dentist or doctor before use.

Keep out of reach of children

If swallowed, get medical help or contact a Poison Control Center right away at 1-800-222-1222.

Inactive ingredient

Water

Other information

Keep tightly closed in a cool dark place • Do not shake bottle • Hold away from face when opening.

For use as an oral debriding agent (oral rinse):

Adults and children 2 years of age and over:
mix with an equal amount of water swish around in the mouth over affected area for at least 1 minute and then spit out. Do not swallow.
Use up to 4 times daily after meals and at bedtime or as directed by a dentist or doctor.
Children under 12 years should be supervised in the use of this product.
Children under 2 years of age: consult a dentist or doctor.